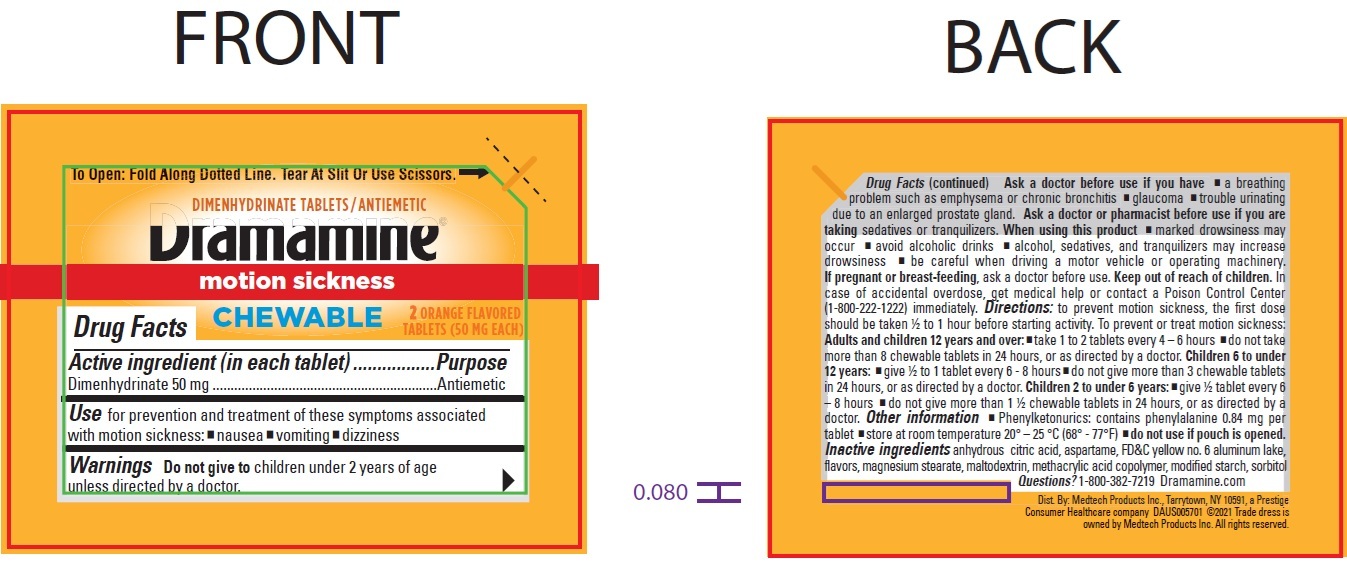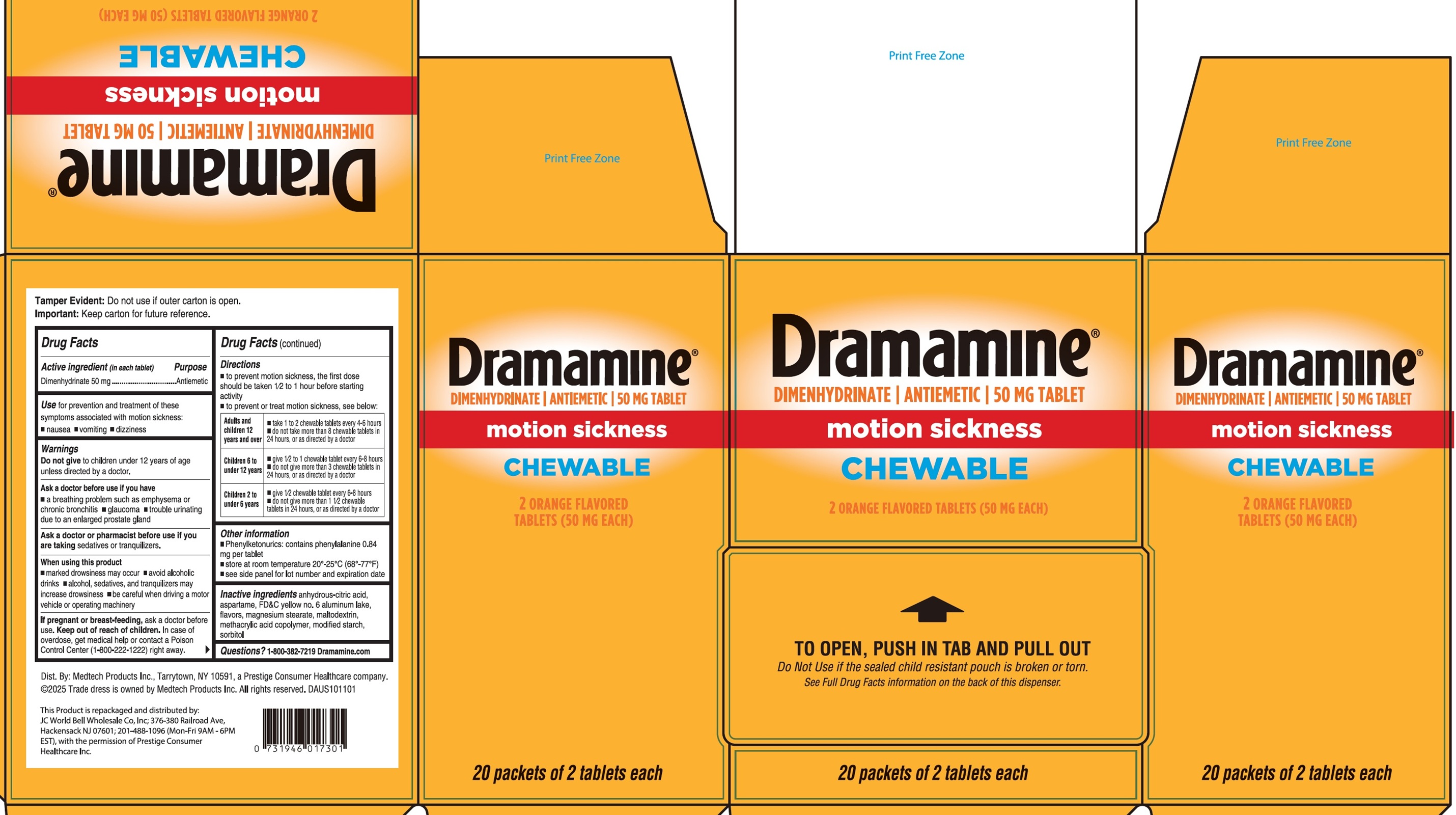 DRUG LABEL: Dramamine Chewable Dimenhydrinate
NDC: 50269-525 | Form: TABLET, CHEWABLE
Manufacturer: JC World Bell Wholesale Co., Inc.
Category: otc | Type: HUMAN OTC DRUG LABEL
Date: 20250903

ACTIVE INGREDIENTS: DIMENHYDRINATE 50 mg/1 1
INACTIVE INGREDIENTS: ANHYDROUS CITRIC ACID; ASPARTAME; FD&C YELLOW NO. 6 ALUMINUM LAKE; MAGNESIUM STEARATE; MALTODEXTRIN; SORBITOL

Dramamine Chewable Dimenhydrinate

Active ingredient (in each tablet)

Dimenhydrinate 50 mg

Purpose

Antiemetic

Use

for prevention and treatment of these symptoms associated with motion sickness:

- nausea
- vomiting
- dizziness

Warnings

Do not givetochildren under 12 years of age unless directed by a doctor.

Ask a doctor before use if you have

- a breathing problem such as emphysema or chronic bronchitis
- glaucoma
- trouble urinating due to an enlarged prostate gland

Ask a doctor or pharmacist before use

if you are taking sedatives or tranquilizers.

When using this product

- marked drowsiness may occur
- avoid alcoholic drinks
- alcohol, sedatives, and tranquilizers may increase drowsiness
- be careful when driving a motor vehicle or operating machinery

If pregnant or breast-feeding,

ask a doctor before use.

Keep out of reach of children.

In case of overdose, get medical help or contact a Poison Control Center (1-800-222-1222) right away.

Directions

- to prevent motion sickness, the first dose should be taken ½ to 1 hour before starting activity
- to prevent or treat motion sickness, see below:

Adults and children 12 years and over | - take 1 to 2 chewable tablets every 4-6 hours - do not take more than 8 chewable tablets in 24 hours, or as directed by a doctor
Children 6 to under 12 years | - give ½ to 1 chewable tablet every 6-8 hours - do not give more than 3 chewable tablets in 24 hours, or as directed by a doctor
Children 2 to under 6 years | - give ½ chewable tablet every 6-8 hours - do not give more than 1 ½ chewable tablets in 24 hours, or as directed by a doctor

Other information

- Phenylketonurics: contains phenylalanine 0.84 mg per tablet
- store at room temperature 20-25ºC (68-77ºF)
- see side panel for lot number and expiration date

Inactive ingredients

anhydrous-citric-acid, aspartame, FD&C yellow no. 6 aluminum lake, flavors, magnesium stearate, maltodextrin, methacrylic acid copolymer, modified starch, sorbitol

Questions?

1-800-382-7219 Dramamine.com